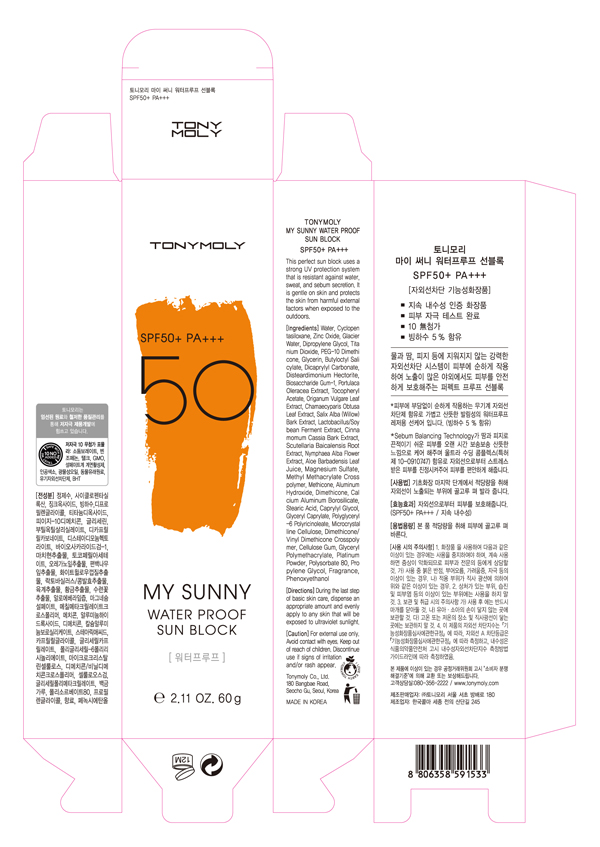 DRUG LABEL: TONYMOLY My Sunny Waterproof Sun Block
NDC: 59078-108 | Form: CREAM
Manufacturer: Tonymoly Co., Ltd.
Category: otc | Type: HUMAN OTC DRUG LABEL
Date: 20160202

ACTIVE INGREDIENTS: ZINC OXIDE 8.064 g/60 g; TITANIUM DIOXIDE 2.106 g/60 g
INACTIVE INGREDIENTS: WILLOW BARK; CYCLOMETHICONE 5; PORTULACA OLERACEA WHOLE; CHAMAECYPARIS OBTUSA LEAF; ALPHA-TOCOPHEROL ACETATE; CELLULOSE, MICROCRYSTALLINE; NYMPHAEA ALBA FLOWER; BUTYLOCTYL SALICYLATE; DICAPRYLYL CARBONATE; BIOSACCHARIDE GUM-1; DISTEARDIMONIUM HECTORITE; WATER; POLYSORBATE 80; MAGNESIUM SULFATE; ALUMINUM HYDROXIDE; PHENOXYETHANOL; STEARIC ACID; CAPRYLYL GLYCOL; GLYCERYL CAPRYLATE; CALCIUM ALUMINUM BOROSILICATE; SCUTELLARIA BAICALENSIS ROOT; ALOE VERA LEAF

Active Ingredients

Dipropylene Glycol 4.00%, Glycerin 2.00%, Titanium Dioxide 3.51%, Zinc Oxide 13.44%

Purpose

Sunscreen SPF50++

Use

This perfect sun block uses a strong UV protection system that is resistant against water, sweat, and sebum secretion. It is gentle on skin and protects the skin from harmful external factors when exposed to the outdoors.

Caution

For external use only. Avoid contact with eyes. Keep out of reach of children. Discontinue use if signs of irritation and/or rash appear.

Keep out of reach of children. Discontinue use if signs of irritation and/or rash appear.

Directions

During the last step of basic skin care, dispense an appropriate amount and evenly apply to any skin that will be exposed to ultraviolet sunlight.

Inactive Ingredients

WATER, CYCLOPENTASILOXANE, PEG-10 DIMETHICONE, BUTYLOCTYL SALICYLATE, DICAPRYLYL CARBONATE, BIOSACCHARIDE GUM-1, DISTEARDIMONIUM HECTORITE, MAGNESIUM SULFATE, METHYL METHACRYLATE CROSSPOLYMER, METHICONE, PORTULACA OLERACEA EXTRACT, ALUMINUM HYDROXIDE, DIMETHICONE, PHENOXYETHANOL, CALCIUM ALUMINUM BOROSILICATE, FRAGRANCE, STEARIC ACID, CAPRYLYL GLYCOL, GLYCERYL CAPRYLATE, POLYGLYCERYL-6 POLYRICINOLEATE, TOCOPHERYL ACETATE, MICROCRYSTALLINE CELLULOSE, DIMETHICONE/VINYL DIMETHICONE CROSSPOLYMER, CHAMAECYPARIS OBTUSA LEAF EXTRACT, ORIGANUM VULGARE LEAF EXTRACT, SALIX ALBA (WILLOW) BARK EXTRACT, CELLULOSE GUM, CINNAMOMUM CASSIA BARK EXTRACT, LACTOBACILLUS/SOYBEAN FERMENT EXTRACT, SCUTELLARIA BAICALENSIS ROOT EXTRACT, NYMPHAEA ALBA FLOWER EXTRACT, ALOE BARBADENSIS LEAF JUICE, GLYCERYL POLYMETHACRYLATE, PROPYLENE GLYCOL, PLATINUM POWDER, POLYSORBATE 80